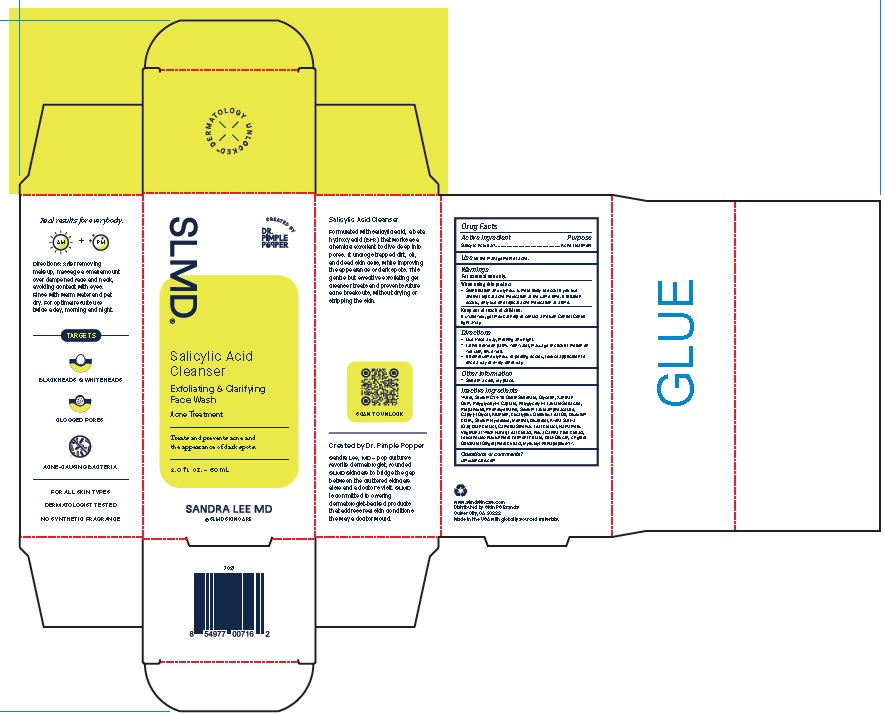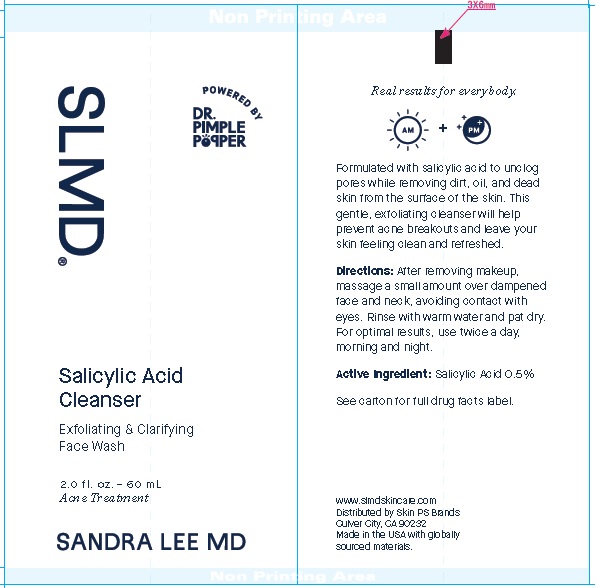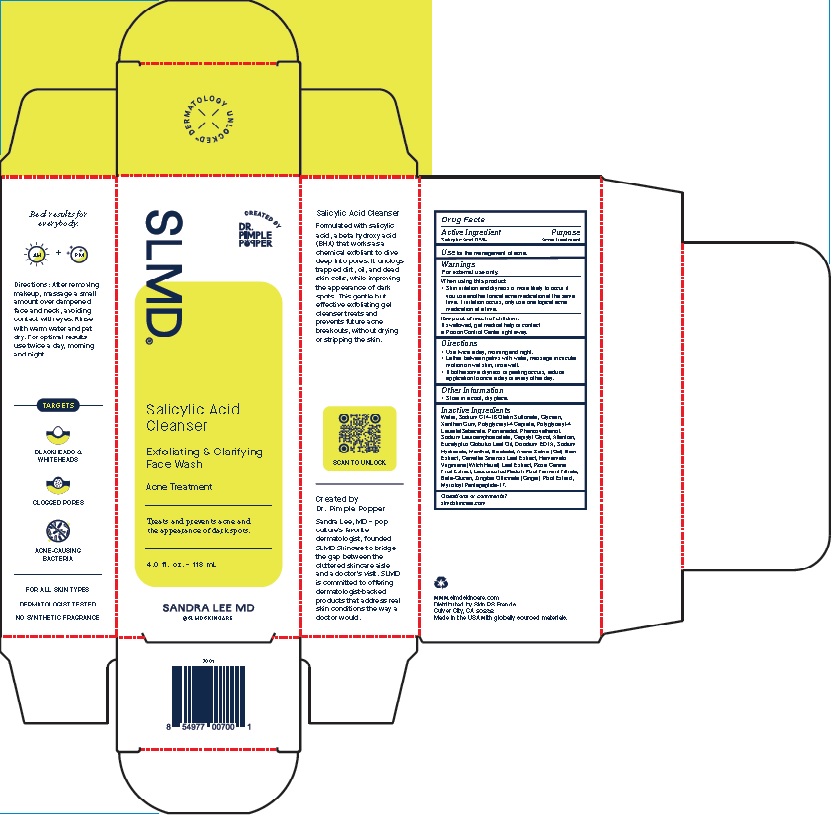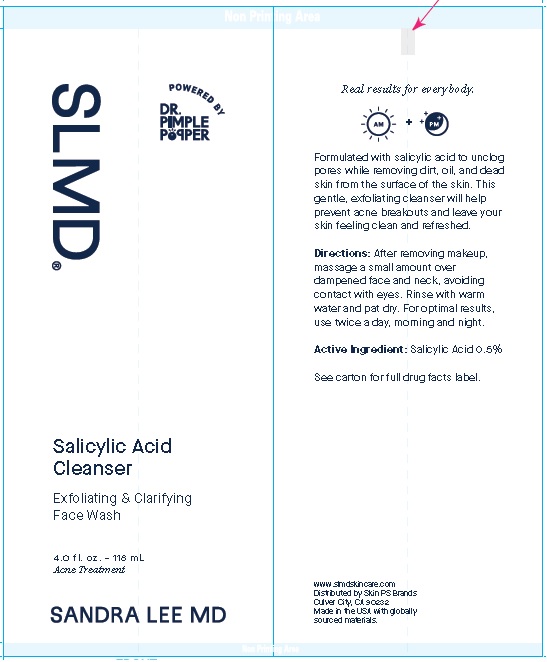 DRUG LABEL: Salicylic Acid Cleanser
NDC: 54111-171 | Form: GEL
Manufacturer: Bentley Laboratories, LLC
Category: otc | Type: HUMAN OTC DRUG LABEL
Date: 20241227

ACTIVE INGREDIENTS: SALICYLIC ACID 5 mg/1 mL
INACTIVE INGREDIENTS: WATER; SODIUM C14-16 OLEFIN SULFONATE; GLYCERIN; XANTHAN GUM; POLYGLYCERYL-4 CAPRATE; PROPANEDIOL; PHENOXYETHANOL; SODIUM LAUROAMPHOACETATE; CAPRYLYL GLYCOL; ALLANTOIN; EUCALYPTUS GLOBULUS LEAF; EDETATE DISODIUM ANHYDROUS; SODIUM HYDROXIDE; MENTHOL; LEVOMENOL; OAT BRAN; GREEN TEA LEAF; HAMAMELIS VIRGINIANA LEAF; ROSA CANINA FRUIT; LEUCONOSTOC/RADISH ROOT FERMENT FILTRATE; TRANSFORMING GROWTH FACTOR BETA RECEPTOR TYPE 3; GINGER; MYRISTOYL PENTAPEPTIDE-4

Salicylic Acid Cleanser

Drug Facts

Active Ingredient
Salicylic Acid 0.5%

Purpose
Acne Treatment

INDICATIONS AND USAGE

Use for the management of acne.

Warnings
For external use only.
When using this product

• Skin irritation and dryness is more likely to occur if you use
another topical acne medication at the same time. If irritation
occurs, only use one topical acne medication at a time.

Keep out of reach of children.

If swallowed, get medical help or contact a Poison Control Center
right away.

Directions
• Use twice a day, morning and night.
• Lather between palms with water, massage in circular motion on
wet skin, rinse well.
• If bothersome dryness or peeling

Other Information
• Store in a cool, dry place.

Inactive Ingredients

Water, Sodium C14-16 Olefin Sulfonate, Glycerin, Xanthan
Gum, Polyglyceryl-4 Caprate, Polyglyceryl-4 Laurate/Sebacate,
Propanediol, Phenoxyethanol, Sodium Lauroamphoacetate,
Caprylyl Glycol, Allantoin, Eucalyptus Globulus Leaf Oil, Disodium
EDTA, Sodium Hydroxide, Menthol, Bisabolol, Avena Sativa
(Oat) Bran Extract, Camellia Sinensis Leaf Extract, Hamamelis
Virginiana (Witch Hazel) Leaf Extract, Rosa Canina Fruit Extract,
Leuconostoc/Radish Root Ferment Filtrate, Beta-Glucan, Zingiber
Officinale (Ginger) Root Extract, Myristoyl Pentapeptide-17.

Questions or comments?
slmdskincare.com

Product Package for Salicylic Acid Cleanser

SLMD®

Salicylic Acid
Cleanser
Exfoliating & Clarifying
Face Wash

Acne Treatment

Treats and prevents acne and
the appearance of dark spots.

2.0 f l. oz. – 60 mL

SANDRA LEE MD

w w w.slmdskincare.com

Distributed by Skin PS Brands
Culver City, CA 90232

Made in the USA with globally sourced materials.

2 Oz.

4 Oz.

res